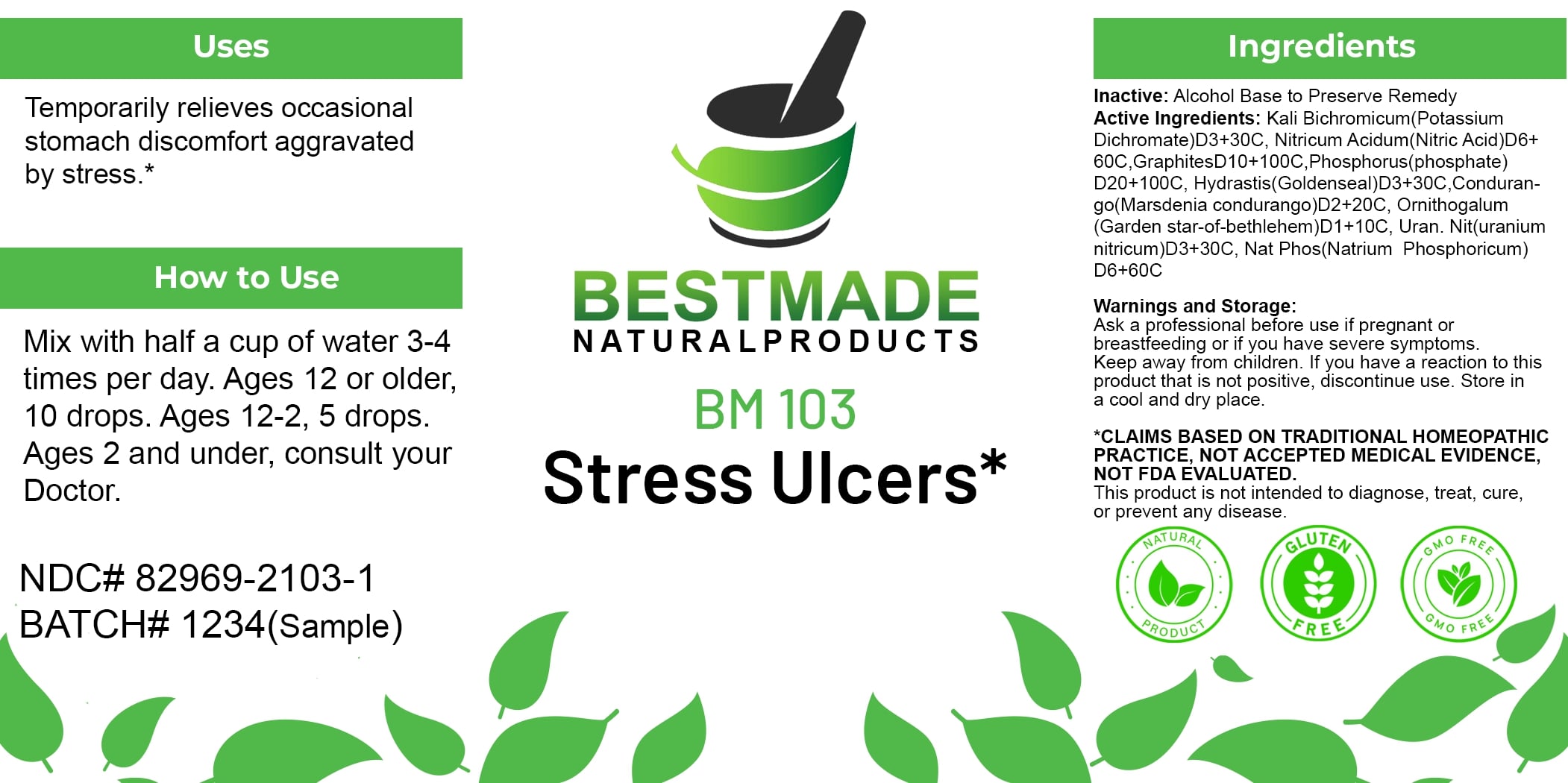 DRUG LABEL: Bestmade Natural Products BM103
NDC: 82969-2103 | Form: LIQUID
Manufacturer: Bestmade Natural Products
Category: homeopathic | Type: HUMAN OTC DRUG LABEL
Date: 20250207

ACTIVE INGREDIENTS: PHOSPHORUS 30 [hp_C]/30 [hp_C]; URANYL NITRATE HEXAHYDRATE 30 [hp_C]/30 [hp_C]; NITRIC ACID 30 [hp_C]/30 [hp_C]; GRAPHITE 30 [hp_C]/30 [hp_C]; SODIUM PHOSPHATE, DIBASIC, HEPTAHYDRATE 30 [hp_C]/30 [hp_C]; GOLDENSEAL 30 [hp_C]/30 [hp_C]; RUEHSSIA CUNDURANGO BARK 30 [hp_C]/30 [hp_C]; POTASSIUM DICHROMATE 30 [hp_C]/30 [hp_C]; ORNITHOGALUM UMBELLATUM 30 [hp_C]/30 [hp_C]
INACTIVE INGREDIENTS: ALCOHOL 30 [hp_C]/30 [hp_C]

BM103

DOSAGE AND ADMINISTRATION

How to Use

Mix with half a cup of water 3-4 times per day. Ages 12 or older, 10 drops. Ages 12-2, 5 drops. Ages 2 and under, consult your Doctor.

INACTIVE INGREDIENT

Ingredients

Inactive: Alcohol Base to Preserve Remedy

ACTIVE INGREDIENT

Active Ingredients: Kali Bichrom (Potassium Dichromate) D3+30C, Arsenicum Alb (Arsenic Oxide) D6+60C, Graphites D10+100C, Phosphorus (Phosphoricum) D20+200C, Hydrastis Can (Golden-Seal) D1+10C, Marsdenia condurango D2+20C, Cimicifuga (Black Cohosh) D3+30C, Natrum Phos (Natrum Phosphoricum) D6+60C

Uses

Temporarily relieves occasional stomach discomfort aggravated by stress.*

*CLAIMS BASED ON TRADITIONAL HOMEOPATHIC PRACTICE, NOT ACCEPTED MEDICAL EVIDENCE, NOT FDA EVALUATED.

This product is not intended to diagnose, treat, cure, or prevent any disease.

Uses

Temporarily relieves occasional stomach discomfort aggravated by stress.*

*CLAIMS BASED ON TRADITIONAL HOMEOPATHIC PRACTICE, NOT ACCEPTED MEDICAL EVIDENCE, NOT FDA EVALUATED.

This product is not intended to diagnose, treat, cure, or prevent any disease.

KEEP OUT OF REACH OF CHILDREN

Warnings and Storage:

Ask a professional before use if pregnant or breastfeeding or if you have severe symptoms. Keep away from children. If you have a reaction to this product that is not positive, discontinue use. Store in a cool and dry place.

Warnings and Storage:

Ask a professional before use if pregnant or breastfeeding or if you have severe symptoms. Keep away from children. If you have a reaction to this product that is not positive, discontinue use. Store in a cool and dry place.

*CLAIMS BASED ON TRADITIONAL HOMEOPATHIC PRACTICE, NOT ACCEPTED MEDICAL EVIDENCE, NOT FDA EVALUATED.

This product is not intended to diagnose, treat, cure, or prevent any disease.

Entire package label